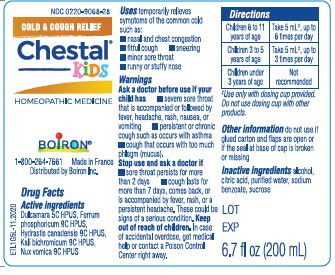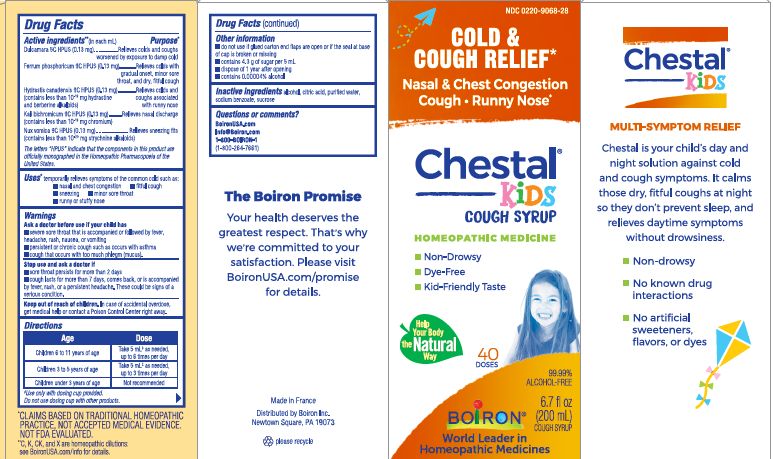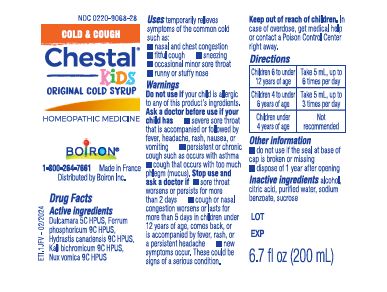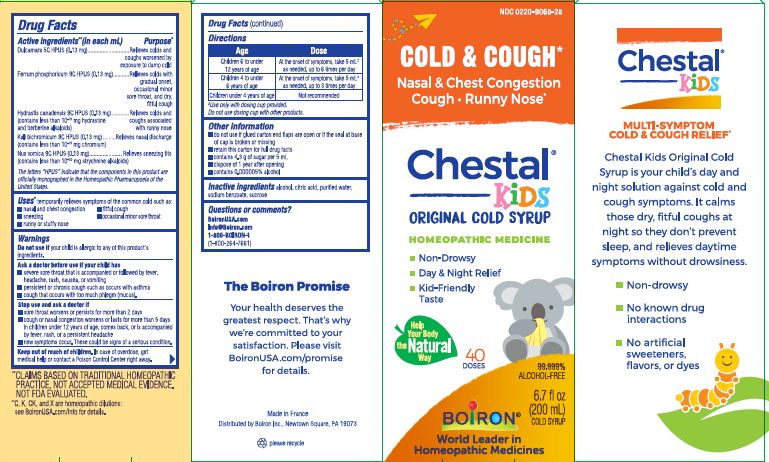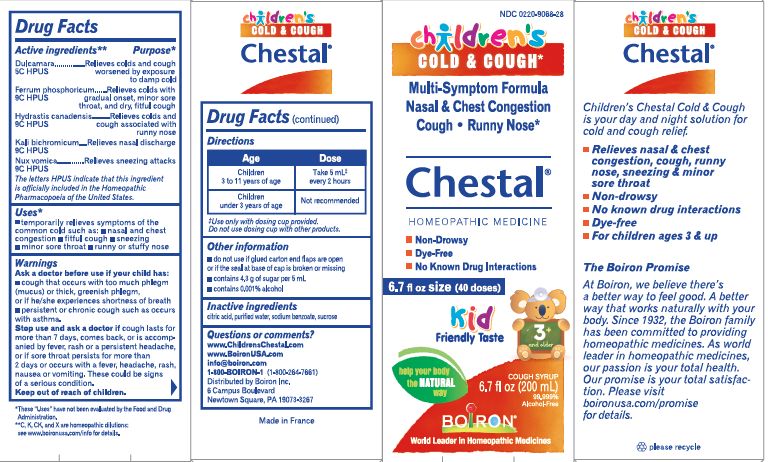 DRUG LABEL: Chestal Childrens Cough and Cold
NDC: 0220-9068 | Form: SYRUP
Manufacturer: Laboratoires Boiron
Category: homeopathic | Type: HUMAN OTC DRUG LABEL
Date: 20240306

ACTIVE INGREDIENTS: SOLANUM DULCAMARA TOP 5 [hp_C]/1 mL; FERRUM PHOSPHORICUM 9 [hp_C]/1 mL; GOLDENSEAL 9 [hp_C]/1 mL; POTASSIUM DICHROMATE 9 [hp_C]/1 mL; STRYCHNOS NUX-VOMICA SEED 9 [hp_C]/1 mL
INACTIVE INGREDIENTS: CITRIC ACID MONOHYDRATE; WATER; SODIUM BENZOATE; SUCROSE; ALCOHOL

Chestal Childrens Cough and Cold

Active ingredients** (in each mL)

Dulcamara 5C HPUS (0.13 mg)

Ferrum phosphoricum 9C HPUS (0.13 mg)

Hydrastis canadensis 9C HPUS (0.13 mg) (contains less than 10^-19 mg hydrastine and berberine alkaloids)

Kali Bichromicum 9C HPUS (0.13 mg) (contains less than 10^-19 mg chromium)

Nux Vomica 9C HPUS (0.13 mg) (contains less than 10^-20 strychnine alkaloids)

The letters "HPUS" indicate that the components in this product are officially monographed in the Homeopathic Pharmacopoeia of the United States.

Purpose*

Dulcamara 5C HPUS ... Relieves cold and coughs worsened by exposure to damp cold

Ferrum phosphoricum 9C HPUS ... Relieves colds with gradual onset, minor sore throat, and dry, fitful cough

Hydrastis canadensis 9C HPUS ... Relieves colds and coughs associated with runny nose

Kali Bichromicum 9C HPUS ... Relieves nasal discharge

Nux Vomica 9C HPUS (0.13mg) ... Relieves sneezing fits

Uses*

temporarily relieves symptoms of the common cold such as:

- nasal and chest congestion
- fitful cough
- sneezing
- occasional minor sore throat
- runny or stuff nose

Do not use if your child is allergic to any of this product's ingredients.

Ask a doctor before use if your child has

- severe sore throat that is accompanied or followed by fever, headache, rash, nausea, or vomiting
- persistent or chronic cough such as occurs with asthma
- cough that occurs with too much phlegm (mucus).

Stop use and ask a doctor if

- sore throat worsens or persists for more than 2 days
- cough or nasal congestion worsens or lasts for more then 5 days in children under 12 years of age, comes back, or is accompanied by fever, rash, or a persistent headache
- new symptoms occur. These could be signs of a serious condition.

Keep out of reach of children. In case of accidental overdose, get medical help or contact a Poison Control Center right away.

Directions

Children 6 to under 12 years of age At the onset of symptoms, take 5 mLǂ as needed, up to 6 times per day

Children 4 to under 6 years of age At the onset of symptoms, take 5 mLǂ as needed, up to 3 times per day

Children under 4 years of age Not recommended

ǂ Use only with dosing cup provided.

Do not use dosing cup with other products.

Other information

do not use if glued carton end flaps are open or if the seal at base of cap is broken or missing

retain this carton for full drug facts
contains 4.3 g of sugar per 5 mL
dispose of 1 year after opening

contains 0.000005% alcohol

40 Doses

6.7 fl oz. (200 mL)

Multi-Symtom Cold & Cough*

Cold & Cough Relief*

Nasal & Chest Congestion Cough Runny Nose*

Non-Drowsy

No known drug interactions

No artifical sweetners, flavors or dyes

Day & Night Relief

Kid-Friendly Taste

*CLAIMS BASED ON TRADITIONAL HOMEOPATHIC PRACTICE NOT ACCEPTED MEDICAL EVIDENCE. NOT FDA EVALUATED.
**C,K,CK, and X are homeopathic dilutions: see BoironUSA.com/info for details.

INACTIVE INGREDIENT

alcohol, citric acid, purified water, sodium benzoate, sucrose

QUESTIONS

BoironUSA.com

Info@boiron.com

1-800-BOIRON-1
(1-800-264-7661),

Made in France

Distributed by Boiron, Inc. Newtown Square, PA 19073